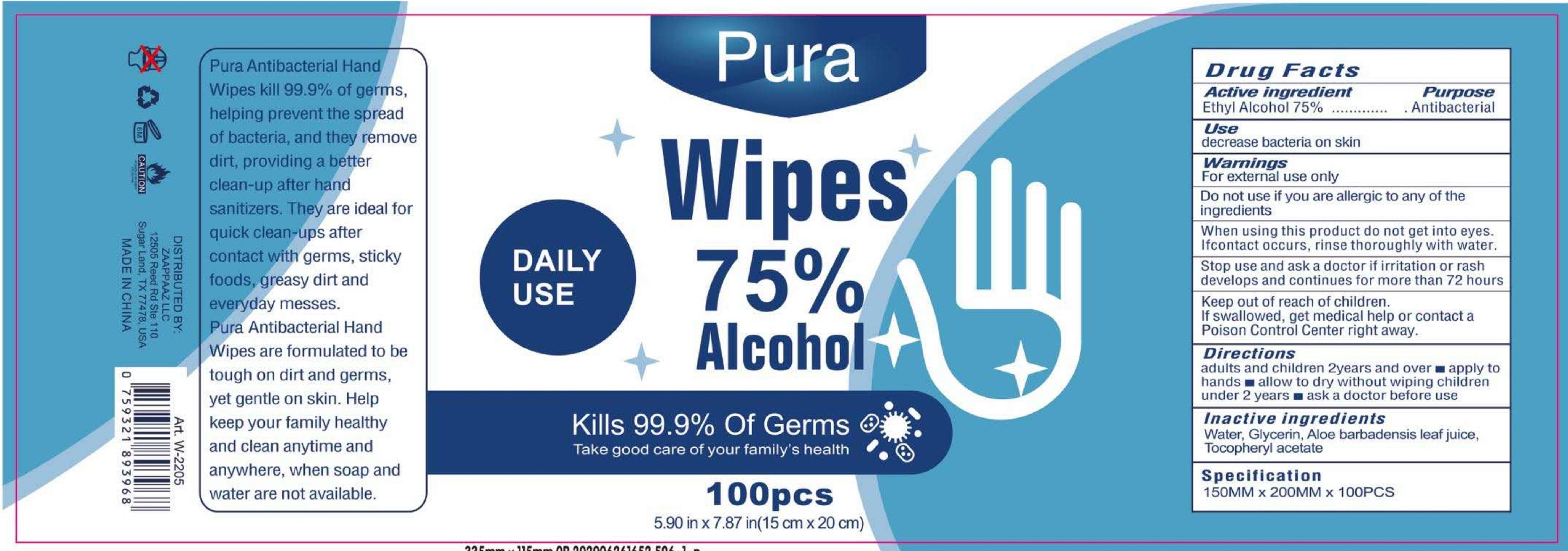 DRUG LABEL: Alcohol disinfection wet wipes
NDC: 79683-001 | Form: CLOTH
Manufacturer: Hefei Inridy Medical Products Co., Ltd
Category: otc | Type: HUMAN OTC DRUG LABEL
Date: 20200717

ACTIVE INGREDIENTS: ALCOHOL 75 1/100 1
INACTIVE INGREDIENTS: GLYCERIN; ALOE VERA LEAF; WATER; .ALPHA.-TOCOPHEROL ACETATE

Alcohol disinfection wet wipes

Active Ingredient(s)

Ethyl Alcohol 75%

Purpose

Antibacterial

Use

decrease bacteria on skin

Warnings

For external use only

Do not use if you are allergic to any of the ingredients

When using this product, do not get into eyes. If contact occurs, rinse thoroughly with water

STOP USE

Stop using and ask a doctor if irritation or rash develops and continues for more than 72 hours

Keep out of reach of children. If swallowed, get medical help or contact a Poison Control Center right away

Directions

adults and children 2years and over
apply to hands
allow to dry without wiping children under 2 years
ask a doctor before use

Other information

/

Inactive ingredients

Water, Glycerin, Aloe barbadensis leaf juice, Tocopheryl acetate